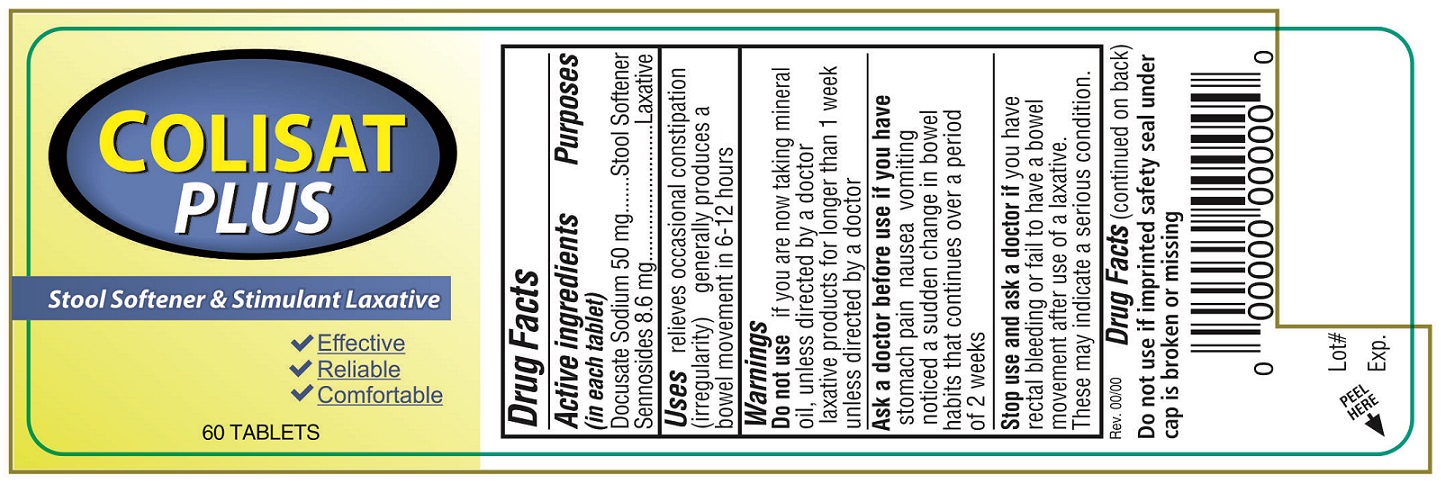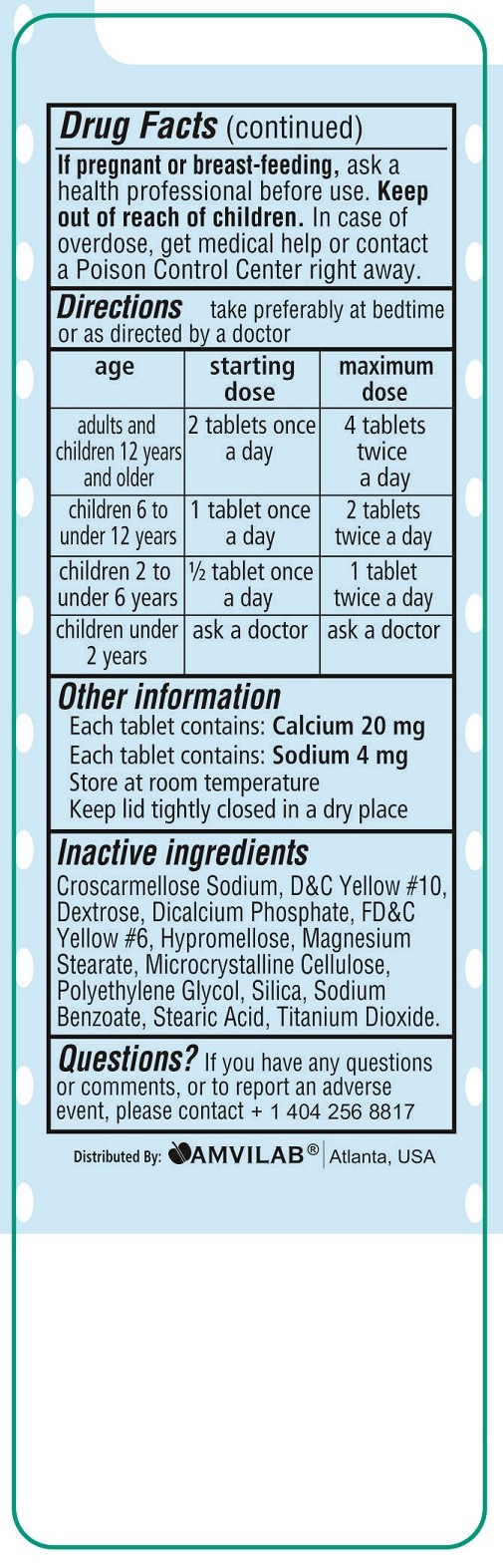 DRUG LABEL: Colistat Plus
NDC: 69975-850 | Form: TABLET, FILM COATED
Manufacturer: Amvilab LLC
Category: otc | Type: HUMAN OTC DRUG LABEL
Date: 20150716

ACTIVE INGREDIENTS: DOCUSATE SODIUM 50 mg/1 1; SENNOSIDES 8.6 mg/1 1
INACTIVE INGREDIENTS: CROSCARMELLOSE SODIUM; D&C YELLOW NO. 10; DEXTROSE; CALCIUM PHOSPHATE, DIBASIC, DIHYDRATE; FD&C YELLOW NO. 6; HYPROMELLOSES; MAGNESIUM STEARATE; CELLULOSE, MICROCRYSTALLINE; POLYETHYLENE GLYCOLS; SILICON DIOXIDE; SODIUM BENZOATE; STEARIC ACID; TITANIUM DIOXIDE

Drug Facts

Active ingredients (in each tablet)

Docusate Sodium 50 mg

Sennosides 8.6 mg

Purposes

Docusate Sodium.............................Stool Softener

Sennosides.......................................Laxative

Uses

- relieves occasional constipation (irregularity)
- generally produces a bowel movement in 6-12 hours

Warnings

Do not use

- if you are now taking mineral oil, unless directed by a doctor
- laxative products for longer than 1 week unless directed by a doctor

Ask a doctor before use if you have

- stomach pain
- nausea
- vomiting
- noticed a sudden change in bowel habits that continues over a period of 2 weeks

Stop use and ask a doctor if

you have rectal bleeding or fail to have a bowel movement after use of a laxative.

These may indicate a serious condition.

If pregnant or breast-feeding,

ask a health professional before use.

Keep out of reach of children.

In case of overdose, get medical help or contact a Poison Control Center right away.

Directions

- take preferably at bedtime or as directed by a doctor

age | starting dose | maximum dose
adults and children 12 years and older | 2 tablets once a day | 4 tablets twice a day
children 6 to under 12 years | 1 tablet once a day | 2 tablets twice a day
children 2 to under 6 years | 1/2 tablet once a day | 1 tablet twice a day
children under 2 years | ask a doctor | ask a doctor

Other information

- Each tablet contains: Calcium 20 mg
- Each tablet contains: Sodium 4 mg
- Store at room temperature
- Keep lid tightly closed in a dry place
- Do not use if imprinted seal under cap is broken or missing
- Tamper Evident: Do not use if sealed blister unit is broken or damaged

Inactive ingredients

Croscarmellose Sodium, D and C Yellow #10, Dextrose, Dicalcium Phosphate, FD and C Yellow #6, Hypromellose, Magnesium Stearate, Microcrystalline Cellulose, Polyethylene Glycol, Silica, Sodium Benzoate, Stearic Acid, Titanium Dioxide.

Questions?

If you have any questions or comments,or to report an adverse event, please contact +1 404 256 8817.

Principal Display Panel

COLISTAT PLUS

Stool Softener and Stimulant Laxative

- Effective
- Reliable
- Comfortable

60 TABLETS